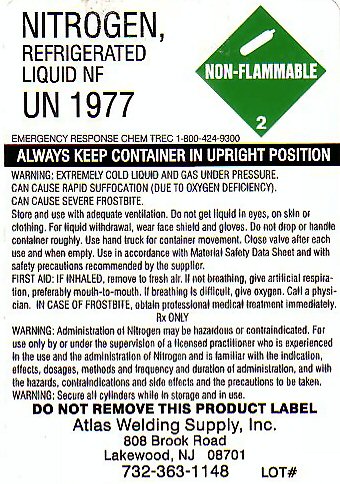 DRUG LABEL: NITROGEN
NDC: 50699-1977 | Form: GAS
Manufacturer: Atlas Welding Supply Co Inc
Category: prescription | Type: HUMAN PRESCRIPTION DRUG LABEL
Date: 20241011

ACTIVE INGREDIENTS: NITROGEN 99 L/100 L

Nitrogen

NITROGEN REFRIGERATED LIQUID LABEL

Nitrogen, Refrigerated Liquid, NF UN1977 NON-FLAMMABLE GAS 2

EMERGENCY RESPONSE CHEM TREC 1-800-424-9300

! ALWAYS KEEP CONTAINER IN UPRIGHT POSITION!

WARNING: EXTREMELY COLD LIQUID AND GAS UNDER PRESSURE. CAN CAUSE RAPID SUFFOCATION (DUE TO OXYGEN DEFICIENCY). CAN CAUSE SEVERE FROSTBITE.

Store and use with adequate ventilation. Do not get liquid in eyes, on skin or clothing. For liquid withdrawal, wear face shield and gloves. Do not drop or handle container roughly. Use hand truck for container movement. Close valve after each use and when empty. Use in accordance with Material Safety Data Sheet and with safety precautions recommended by the supplier.

FIRST AID: IF INHALED: remove to fresh air. If not breathing, give artificial resuscitation, preferably by mouth-to-mouth. If breathing is difficult, give oxygen. Call a physician. IN CASE OF FROTBITE, obtain professional medical treatment immediately.

Rx ONLY.

WARNING: Administration of Nitrogen may be hazardous or contraindicated. For use only by or under the supervision of a licensed practitioner who is experienced in the use and administration of Nitrogen and is familiar with the indications, effects, dosages, methods, and frequency and duration of administration, and with the hazards, contraindications, and side effects, and the precautions to be taken. WARNING: Secure all cylinders while in storage and in use.

DO NOT REMOVE THIS PRODUCT LABEL

Atlas Welding Supply, Inc

808 Brook Road

Lakewood, NJ 08701

732-363-1148 Lot#